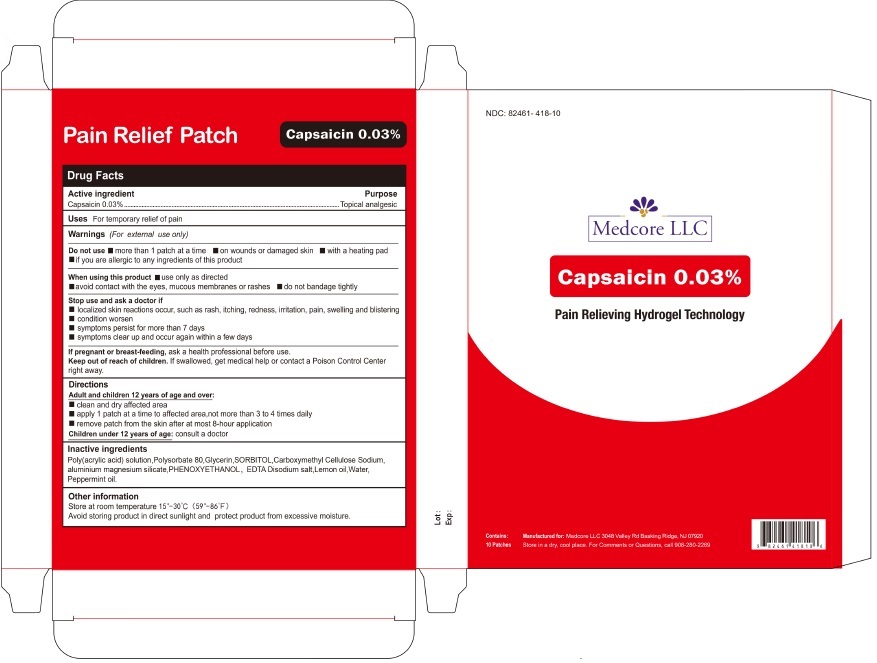 DRUG LABEL: Capsaicin 0.03% Patch
NDC: 82461-418 | Form: PATCH
Manufacturer: Medcore LLC
Category: otc | Type: HUMAN OTC DRUG LABEL
Date: 20251104

ACTIVE INGREDIENTS: CAPSAICIN 0.03 g/100 g
INACTIVE INGREDIENTS: ACRYLIC ACID; POLYSORBATE 80; GLYCERIN; SORBITOL; CARBOXYMETHYLCELLULOSE SODIUM, UNSPECIFIED; MAGNESIUM ALUMINUM SILICATE; PHENOXYETHANOL; EDETATE DISODIUM; LEMON OIL, COLD PRESSED; WATER; PEPPERMINT OIL

Pain Relief Patch Capsaicin 0.03%

Drug Facts

Active ingredient

Capsaicin 0.03%

Purpose

Topical analgesic

Uses

For temporary relief of pain

Warnings

(For external use only)

Do not use

- more than 1 patch at a time
- on wounds or damaged skin
- with a heating pad
- if you are allergic to any ingredients of this product

When using this product

- use only as directed
- avoid contact with the eyes, mucous membranes or rashes
- do not bandage tightly

Stop use and ask a doctor if

- localized skin reactions occur, such as rash, itching, redness, irritation, pain, swelling and blistering
- condition worsen
- symptoms persist for more than 7 days
- symptoms clear up and occur again within a few days

PREGNANCY OR BREAST FEEDING

If pregnant or breast-feeding, ask a health professional before use.

Keep out of reach of children. If swallowed, get medical help or contact a Poison Control Center right away.

Directions

Adult and children 12 years of age and over:

- clean and dry affected area
- apply 1 patch at a time to affected area,not more than 3 to 4 times daily
- remove patch from the skin after at most 8-hour application

Children under 12 years of age: consult a doctor

Inactive ingredients

Poly(acrylic acid) solution,Polysorbate 80,Glycerin,SORBITOL,Carboxymethyl Cellulose Sodium, aluminium magnesium silicate,PHENOXYETHANOL, EDTA Disodium salt,Lemon oil,Water, Peppermint oil.

Other information

Store at room temperature 15°-30°C (59°-86°F)
Avoid storing product in direct sunlight and protect product from excessive moisture.

PRINCIPAL DISPLAY PANEL

NDC: 82461- 418-10

Medcore LLC

Capsaicin 0.03%

Pain Relieving Hydrogel Technology

Contains:

10 Patches

Manufactured for: Medcore LLC 3048 Valley Rd Basking Ridge, NJ 07920

Store in a dry, cool place. For Comments or Questions, call 908-280-2269